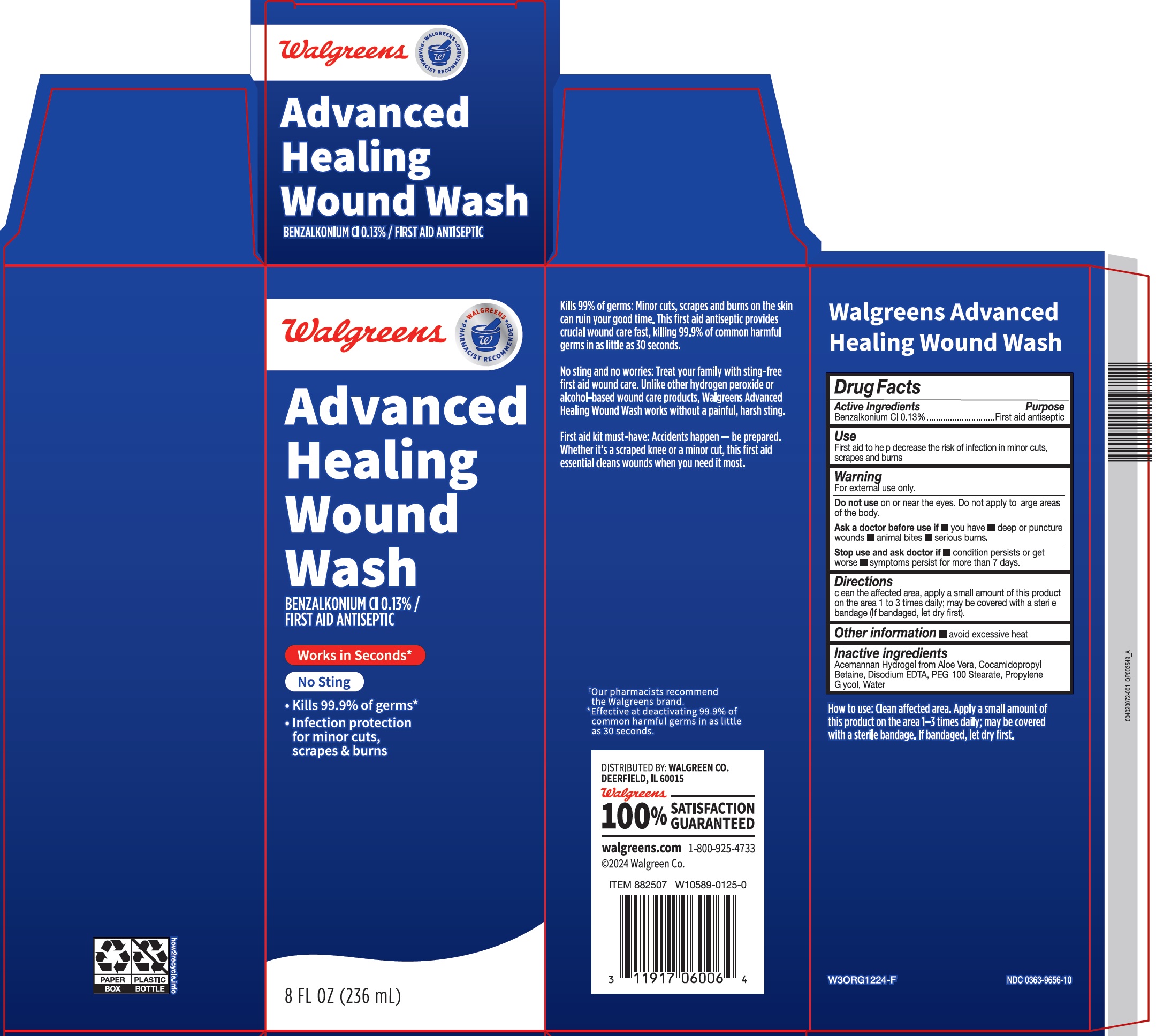 DRUG LABEL: Walgreens Advanced Wound Wash
NDC: 0363-9656 | Form: LIQUID
Manufacturer: Walgreens Co.
Category: otc | Type: HUMAN OTC DRUG LABEL
Date: 20250520

ACTIVE INGREDIENTS: BENZALKONIUM CHLORIDE 1.3 mg/1 mL
INACTIVE INGREDIENTS: COCAMIDOPROPYL BETAINE; EDETATE DISODIUM; PEG-100 MONOSTEARATE; PROPYLENE GLYCOL; WATER

Walgreens Advanced Wound Wash

Active Ingredients

Benzalkonium Cl 0.13%

Purpose

First aid antiseptic

Use

First aid to help decrease the risk of infection in minor cuts, scrapes and burns

Warnings:

For external use only.

Do not use

Do not apply to large areas of the body.

Ask a doctor before use if

- you have
- deep or puncture wounds
- animal bites
- serious burns.

Stop use and ask a doctor if:

- condition persists or get worse
- symptoms persist for more than 7 days.

Directions:

clean the affected area, apply a small amount of this product on the area 1 to 3 times daily; may be covered with a sterile bandage (If bandaged, let dry first).

Other information:

- avoid excessive heat

Inactive ingredients:

Acemannan Hydrogel from aloe Vera, Cocamidopropyl Betaine, Disodium EDTA, PEG-100 Stearate, Propylene Glycol, Water